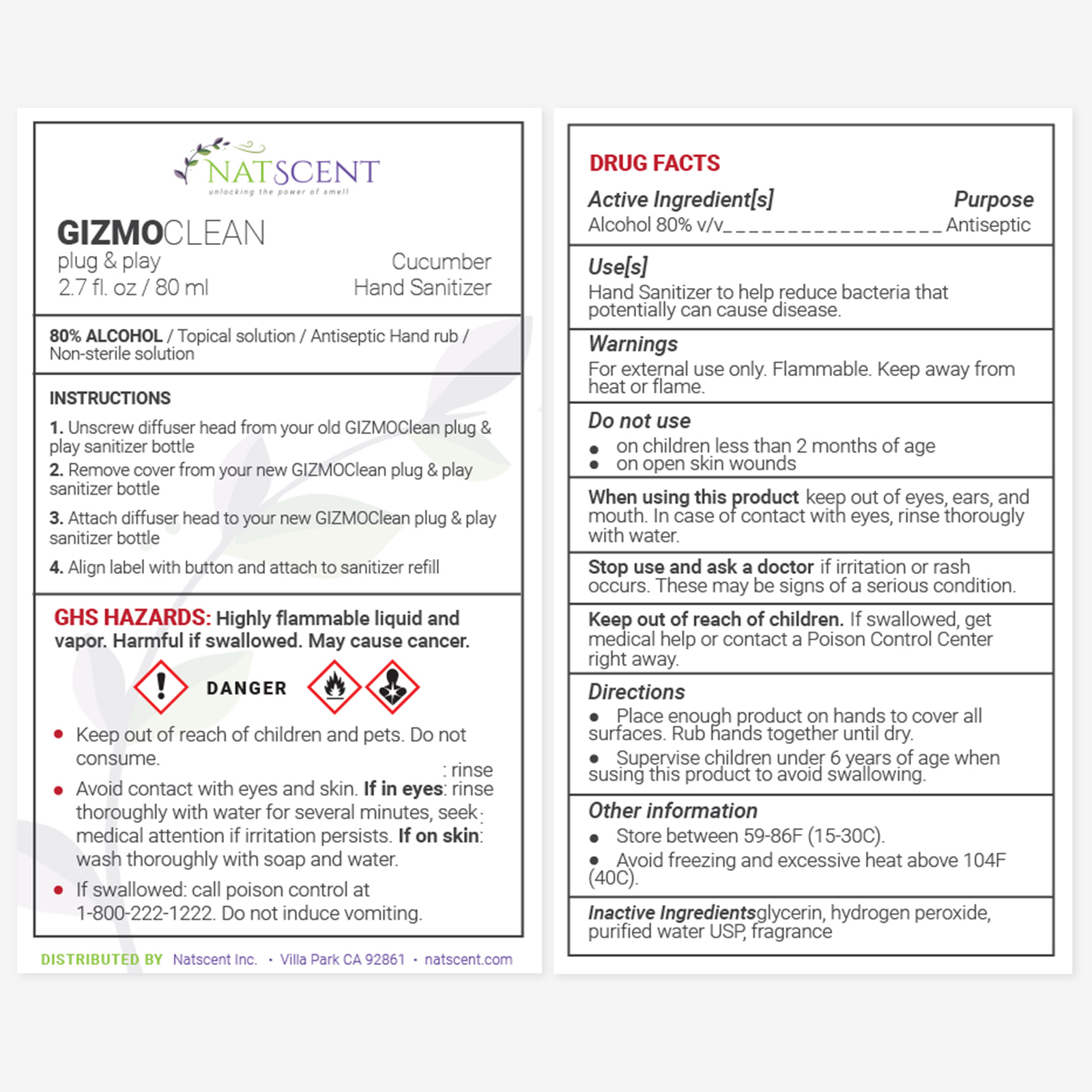 DRUG LABEL: GIZMOCLEAN
NDC: 83026-111 | Form: SPRAY
Manufacturer: Natscent Inc
Category: otc | Type: HUMAN OTC DRUG LABEL
Date: 20221003

ACTIVE INGREDIENTS: ALCOHOL 80 mL/100 mL
INACTIVE INGREDIENTS: CUCUMBER FRUIT OIL; GLYCERIN; HYDROGEN PEROXIDE; WATER

Natscent- Alpha Sanitizer Cucumber

Active Ingredient(s)

Alcohol 80% v/v. Purpose: Antiseptic

Purpose

Antiseptic, Hand Sanitizer

Use

Hand Sanitizer to help reduce bacteria that potentially can cause disease.

Warnings

For external use only. Flammable. Keep away from heat or flame

Do not use

- in children less than 2 months of age
- on open skin wounds

WHEN USING

keep out of eyes, ears, and mouth

In case of contact with eyes, rinse thorougly with water

Stop use and ask a doctor if irritation or rash occurs. These may be signs of a serious condition.

Keep out of reach of children. If swallowed, get medical help or contact a Poison Control Center right away.

Directions

- Place enough product on hands to cover all surfaces. Rub hands together until dry.
- Supervise children under 6 years of age when susing this product to avoid swallowing.

Other information

Store between 59-86F (15-30C). • Avoid freezing and excessive heat above 104F (40C).

Inactive ingredients

glycerin, hydrogen peroxide, purified water USP, fragrance

Package Label - Principal Display Panel

80 mL NDC 83026-111-12